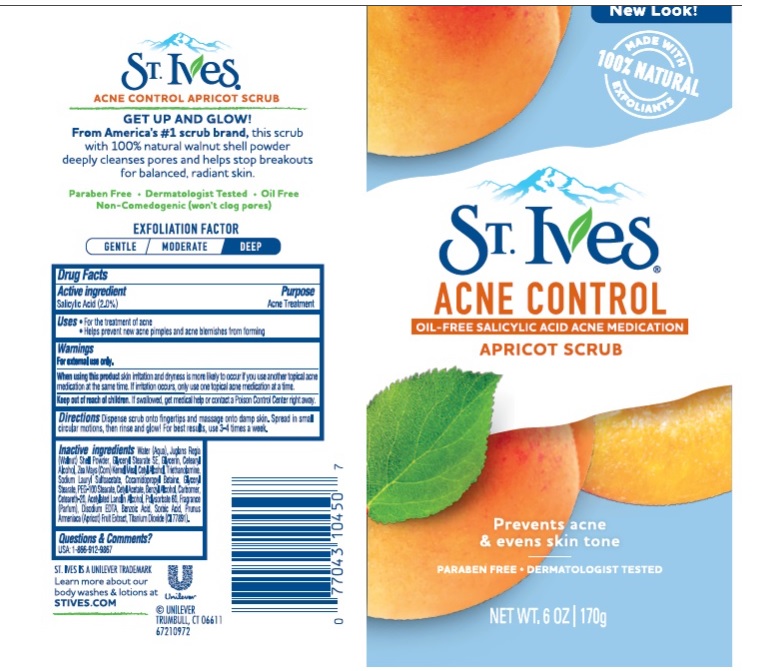 DRUG LABEL: St. Ives
NDC: 64942-1859 | Form: EMULSION
Manufacturer: CONOPCO Inc. d/b/a Unilever
Category: otc | Type: HUMAN OTC DRUG LABEL
Date: 20241107

ACTIVE INGREDIENTS: SALICYLIC ACID 0.02 g/1 g
INACTIVE INGREDIENTS: WATER; JUGLANS REGIA SHELL; GLYCERIN; SODIUM LAURYL SULFOACETATE; GLYCERYL MONOSTEARATE; CORN GRAIN; COCAMIDOPROPYL BETAINE; CETOSTEARYL ALCOHOL; TROLAMINE; CETYL ALCOHOL; PEG-100 STEARATE; APRICOT; CETYL ACETATE; POLYOXYL 20 CETOSTEARYL ETHER; TITANIUM DIOXIDE; POLYSORBATE 60; BENZYL ALCOHOL; EDETATE DISODIUM ANHYDROUS; ACETYLATED LANOLIN ALCOHOLS; BENZOIC ACID; SORBIC ACID; CARBOMER HOMOPOLYMER, UNSPECIFIED TYPE; GLYCERYL STEARATE SE

St. Ives Acne Control Apricot Scrub

ST. IVES ACNE CONTROL APRICOT SCRUB - (salicylic acid) emulsion

St. Ives Acne Control Apricot Scrub

Active ingredient

Salicylic Acid (2%)

Purpose

Acne Treatment

Uses

· For the treatment of acne

Helps prevent new acne pimples and acne blemishes from forming

Warnings

For external use only
When using this product skin irritation and dryness is more likely to occur if you use another topical acne medication at the same time. If irritation occues, only use one topical acne medication at a time.
When using this product keep out of eyes. Rinse with water to remove

Keep out of reach of children
If swallowed, get medical help or contact a Poison Control Center right away.

Directions

Dispense scrub onto fingertips and massage onto damp skin. Spread in small circular motions, then rinse and glow! For best results, use 3-4 times a week

Inactive ingredients

Water (Aqua), Juglans Regia (Walnut) Shell Powder, Glyceryl Stearate SE, Glycerin, Cetearyl Alcohol, Zea Mays (Corn) Kernel Meal, Cetyl Alcohol, Triethanolamine, Sodium Lauryl Sulfoacetate, Cocamidopropyl Betaine, Glyceryl Stearate, PEG-100 Stearate, Cetyl Acetate, Benzyl Alcohol, Carbomer, Ceteareth-20, Acetylated Lanolin Alcohol, Polysorbate 60, Fragrance (Parfum), Disodium EDTA, Benzoic Acid, Sorbic Acid, Prunus Armeniaca (Apricot) Fruit Extract, Titanium Dioxide (CI 77891).

Questions or comments?

USA: 1-800-912-9867